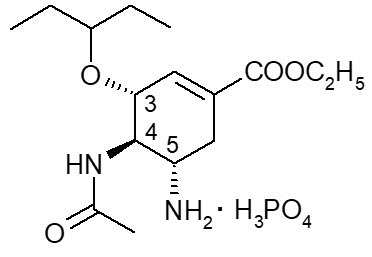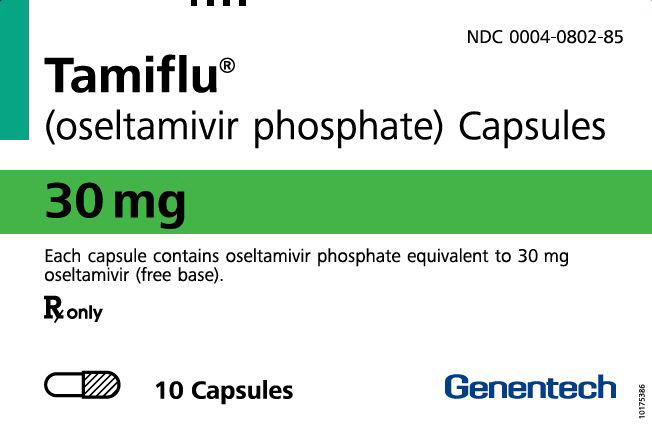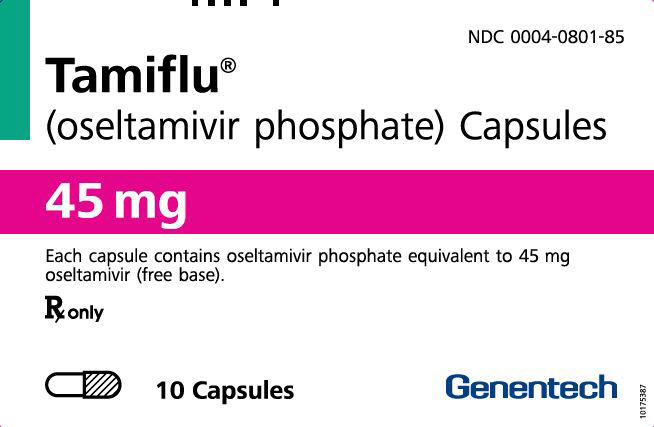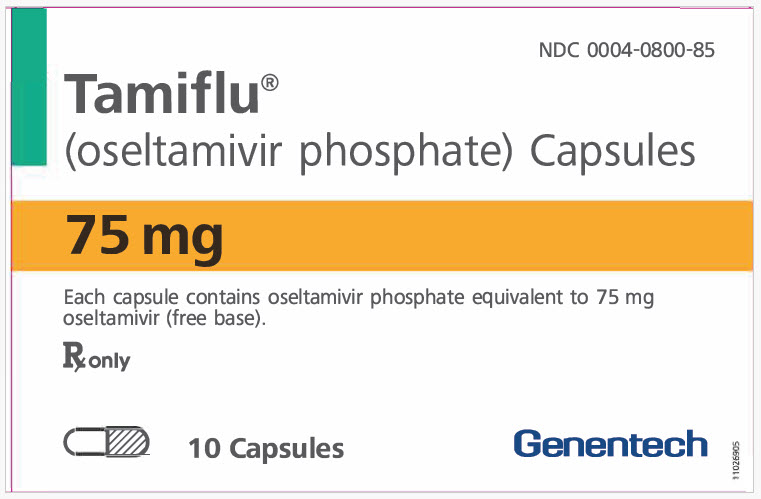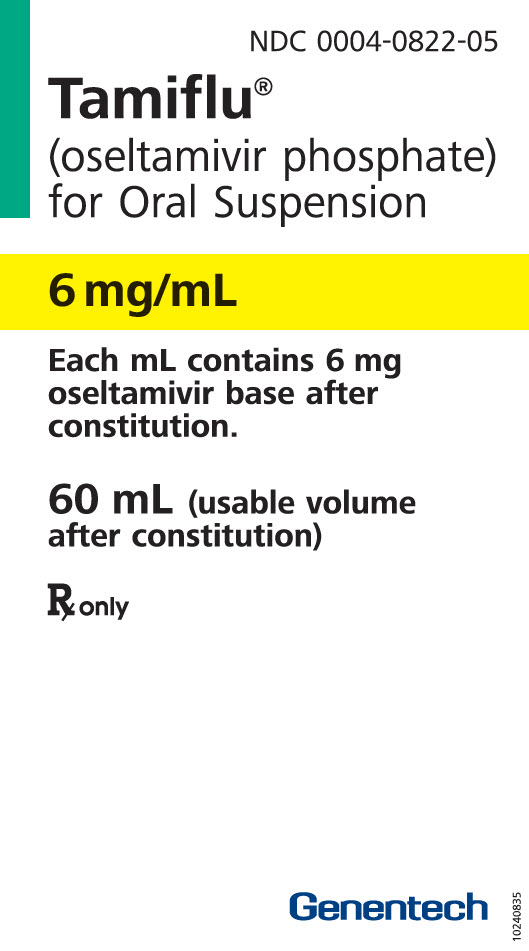 DRUG LABEL: Tamiflu
NDC: 0004-0802 | Form: CAPSULE
Manufacturer: Genentech, Inc.
Category: prescription | Type: HUMAN PRESCRIPTION DRUG LABEL
Date: 20251215

ACTIVE INGREDIENTS: OSELTAMIVIR PHOSPHATE 30 mg/1 1
INACTIVE INGREDIENTS: STARCH, CORN; POVIDONE K30; CROSCARMELLOSE SODIUM; TALC; SODIUM STEARYL FUMARATE; GELATIN, UNSPECIFIED; TITANIUM DIOXIDE; FERRIC OXIDE YELLOW; FERRIC OXIDE RED; FD&C BLUE NO. 2; SHELLAC

HIGHLIGHTS OF PRESCRIBING INFORMATION

These highlights do not include all the information needed to use TAMIFLU safely and effectively. See full prescribing information for TAMIFLU.
TAMIFLU® (oseltamivir phosphate) capsules, for oral use
TAMIFLU® (oseltamivir phosphate) for oral suspension
Initial U.S. Approval: 1999

1 INDICATIONS AND USAGE

TAMIFLU is an influenza neuraminidase inhibitor (NAI) indicated for:

- Treatment of acute, uncomplicated influenza A and B in patients 2 weeks of age and older who have been symptomatic for no more than 48 hours. (1.1)
- Prophylaxis of influenza A and B in patients 1 year and older. (1.2)

Limitations of Use:

- Not a substitute for annual influenza vaccination. (1.3)
- Consider available information on influenza drug susceptibility patterns and treatment effects when deciding whether to use. (1.3)
- Not recommended for patients with end-stage renal disease not undergoing dialysis. (1.3)

2 DOSAGE AND ADMINISTRATION

Treatment of influenza

- Adults and adolescents (13 years and older): 75 mg twice daily for 5 days (2.2)
- Pediatric patients 1 to 12 years of age: Based on weight twice daily for 5 days (2.2)
- Pediatric patients 2 weeks to less than 1 year of age: 3mg/kg twice daily for 5 days (2.2)
- Renally impaired adult patients (creatinine clearance >30-60 mL/min): Reduce to 30 mg twice daily for 5 days (2.4)
- Renally impaired adult patients (creatinine clearance >10-30 mL/min): Reduce to 30 mg once daily for 5 days (2.4)
- ESRD patients on hemodialysis: Reduce to 30 mg immediately and then 30 mg after every hemodialysis cycle. Treatment duration not to exceed 5 days (2.4)
- ESRD patients on CAPD: Reduce to a single 30 mg dose immediately (2.4)

Prophylaxis of influenza

- Adults and adolescents (13 years and older): 75 mg once daily for at least 10 days (2.3)
  - Community outbreak: 75 mg once daily for up to 6 weeks (2.3)
- Pediatric patients 1 to 12 years of age: Based on weight once daily for 10 days (2.3)
  - Community outbreak: Based on weight once daily for up to 6 weeks (2.3)
- Renally impaired adult patients (creatinine clearance >30-60 mL/min): Reduce to 30 mg once daily (2.4)
- Renally impaired adult patients (creatinine clearance >10-30 mL/min): Reduce to 30 mg once every other day (2.4)
- ESRD patients on hemodialysis: Reduce to 30 mg immediately and then 30 mg after alternate hemodialysis cycles for the recommended duration of prophylaxis (2.4)
- ESRD patients on CAPD: Reduce to 30 mg immediately and then 30 mg once weekly for the recommended duration of prophylaxis (2.4)

3 DOSAGE FORMS AND STRENGTHS

- Capsules: 30 mg, 45 mg, 75 mg (3)
- For oral suspension: 360 mg oseltamivir base supplied as powder (constituted to a final concentration of 6 mg/mL) (3)

4 CONTRAINDICATIONS

Patients with known serious hypersensitivity to oseltamivir or any of the components of TAMIFLU (4)

5 WARNINGS AND PRECAUTIONS

- Serious skin/hypersensitivity reactions such as Stevens-Johnson Syndrome, toxic epidermal necrolysis and erythema multiforme: Discontinue TAMIFLU and initiate appropriate treatment if allergic-like reactions occur or are suspected. (5.1)
- Neuropsychiatric events: Patients with influenza, including those receiving TAMIFLU, particularly pediatric patients, may be at an increased risk of confusion or abnormal behavior early in their illness. Monitor for signs of abnormal behavior. (5.2)

6 ADVERSE REACTIONS

Most common adverse reactions (>1% and more common than with placebo):

- Treatment studies – Nausea, vomiting, headache. (6.1)
- Prophylaxis studies – Nausea, vomiting, headache, pain. (6.1)

To report SUSPECTED ADVERSE REACTIONS, contact Genentech at 1-888-835-2555 or FDA at 1-800-FDA-1088 or www.fda.gov/medwatch

7 DRUG INTERACTIONS

Live attenuated influenza vaccine (LAIV), intranasal:

Avoid administration of LAIV within 2 weeks before or 48 hours after TAMIFLU use, unless medically indicated. (7)

FULL PRESCRIBING INFORMATION

1 INDICATIONS AND USAGE

1.1 Treatment of Influenza

TAMIFLU is indicated for the treatment of acute, uncomplicated illness due to influenza A and B infection in patients 2 weeks of age and older who have been symptomatic for no more than 48 hours.

1.2 Prophylaxis of Influenza

TAMIFLU is indicated for the prophylaxis of influenza A and B in patients 1 year and older.

1.3 Limitations of Use

- TAMIFLU is not a substitute for early influenza vaccination on an annual basis as recommended by the Centers for Disease Control and Prevention Advisory Committee on Immunization Practices.
- Influenza viruses change over time. Emergence of resistance substitutions could decrease drug effectiveness. Other factors (for example, changes in viral virulence) might also diminish clinical benefit of antiviral drugs. Prescribers should consider available information on influenza drug susceptibility patterns and treatment effects when deciding whether to use TAMIFLU [see Microbiology (12.4)].
- TAMIFLU is not recommended for patients with end-stage renal disease not undergoing dialysis [see Dosage and Administration (2.4) and Use in Specific Populations (8.6)].

2 DOSAGE AND ADMINISTRATION

2.1 Dosage and Administration Overview

Administer TAMIFLU for the treatment of influenza in patients 2 weeks of age or older [see Dosage and Administration (2.2)] or for prophylaxis of influenza in patients 1 year and older [see Dosage and Administration (2.3)] using:

- TAMIFLU capsules or
- TAMIFLU for oral suspension (supplied as a powder). This is the preferred formulation (6 mg per mL) for patients who cannot swallow capsules. Prior to use, the supplied TAMIFLU powder must be constituted with water by the pharmacist to produce the oral suspension [see Dosage and Administration (2.5)].

The capsules and oral suspension may be taken with or without food; however, tolerability may be enhanced if TAMIFLU is taken with food.

Adjust the TAMIFLU dosage in patients with moderate or severe renal impairment [see Dosage and Administration (2.4)].

For patients who cannot swallow capsules, TAMIFLU for oral suspension is the preferred formulation. When TAMIFLU for oral suspension is not available from wholesaler or the manufacturer, TAMIFLU capsules may be opened and mixed with sweetened liquids such as regular or sugar-free chocolate syrup, corn syrup, caramel topping, or light brown sugar (dissolved in water). During emergency situations and when neither the oral suspension or the age-appropriate strengths of TAMIFLU capsules to mix with sweetened liquids are available, then a pharmacist may prepare an emergency supply of oral suspension from TAMIFLU 75 mg capsules [see Dosage and Administration (2.6)].

2.2 Recommended Dosage for Treatment of Influenza

Initiate treatment with TAMIFLU within 48 hours of influenza symptom onset.

Adults and Adolescents (13 years of age and older)

The recommended oral dosage of TAMIFLU for treatment of influenza in adults and adolescents 13 years and older is 75 mg twice daily (one 75 mg capsule or 12.5 mL of oral suspension twice daily) for 5 days.

Pediatric Patients (2 weeks of age through 12 years of age)

Table 1 displays the recommended oral dosage of TAMIFLU for treatment of influenza in pediatric patients 2 weeks of age through 12 years of age and provides information about prescribing the capsule or the formulation for oral suspension.

2.3 Recommended Dosage for Prophylaxis of Influenza

Initiate post-exposure prophylaxis with TAMIFLU within 48 hours following close contact with an infected individual. Initiate seasonal prophylaxis with TAMIFLU during a community outbreak.

Adults and Adolescents (13 years of age and older)

The recommended dosage of TAMIFLU for prophylaxis of influenza in adults and adolescents 13 years and older is 75 mg orally once daily (one 75 mg capsule or 12.5 mL of oral suspension once daily) for at least 10 days following close contact with an infected individual and up to 6 weeks during a community outbreak. In immunocompromised patients, TAMIFLU may be continued for up to 12 weeks [see Use in Specific Populations (8.9)]. The duration of protection lasts for as long as TAMIFLU dosing is continued.

Pediatric Patients (1 year to 12 years of age)

Table 1 displays the recommended oral dosage of TAMIFLU for prophylaxis of influenza in pediatric patients 1 year to 12 years of age based on body weight and provides information about prescribing the capsule or the formulation for oral suspension. Prophylaxis in pediatric patients is recommended for 10 days following close contact with an infected individual and up to 6 weeks during a community outbreak [see Use in Specific Populations (8.4) and Clinical Studies (14.2)].

Table 1 TAMIFLU Dosage Recommendations in Pediatric Patients for Treatment and Prophylaxis of Influenza
Weight | Treatment Dosage for 5 days | Prophylaxis Dosage for 10 days [The recommended duration for post-exposure prophylaxis is 10 days and the recommended duration for community outbreak (seasonal/pre-exposure) prophylaxis is up to 6 weeks (or up to 12 weeks in immunocompromised patients). The amount supplied (e.g., number of bottles or capsules) for seasonal prophylaxis may be greater than for post-exposure prophylaxis.] | Volume of Oral Suspension (6 mg/mL) for each Dose [Use an oral dosing dispensing device that measures the appropriate volume in mL with the oral suspension.] | Number of Bottles of Oral Suspension to Dispense | Number of Capsules to Dispense (Strength) [TAMIFLU for oral suspension is the preferred formulation for patients who cannot swallow capsules.]
Patients from 2 Weeks to less than 1 Year of Age
Any weight | 3 mg/kg twice daily | Not applicable | 0.5 mL/kg [For patients less than 1 year of age, provide an appropriate dosing device that can accurately measure and administer small volumes.] | 1 bottle | Not applicable
Patients 1 to 12 Years of Age Based on Body Weight
15 kg or less | 30 mg twice daily | 30 mg once daily | 5 mL | 1 bottle | 10 capsules (30 mg)
15.1 kg to 23 kg | 45 mg twice daily | 45 mg once daily | 7.5 mL | 2 bottles | 10 capsules (45 mg)
23.1 kg to 40 kg | 60 mg twice daily | 60 mg once daily | 10 mL | 2 bottles | 20 capsules (30 mg)
40.1 kg or more | 75 mg twice daily | 75 mg once daily | 12.5 mL | 3 bottles | 10 capsules (75 mg)

2.4 Dosage in Patients with Renal Impairment

Table 2 displays the dosage recommendations for the treatment and prophylaxis of influenza in adults with various stages of renal impairment (estimated creatinine clearance of less than or equal to 90 mL per minute). Dosage modifications are recommended in adults with an estimated creatinine clearance less than or equal to 60 mL per minute [see Use in Specific Population (8.6) and Clinical Pharmacology (12.3)].

Table 2 Recommended Dosage Modifications for Treatment and Prophylaxis of Influenza in Adults with Renal Impairment or End Stage Renal Disease (ESRD) on Dialysis
Renal Impairment (Creatinine Clearance) | Recommended Treatment Regimen [Capsules or oral suspension can be used for 30 mg dosing.] | Recommended Prophylaxis Regimen [The recommended duration for post-exposure prophylaxis is at least 10 days and the recommended duration for community outbreak (seasonal/pre-exposure) prophylaxis is up to 6 weeks (or up to 12 weeks in immunocompromised patients).]
Mild (>60-90 mL/minute) | 75 mg twice daily for 5 days | 75 mg once daily
Moderate (>30-60 mL/minute) | 30 mg twice daily for 5 days | 30 mg once daily
Severe (>10-30 mL/minute) | 30 mg once daily for 5 days | 30 mg every other day
ESRD Patients on Hemodialysis (≤ 10 mL/minute) | 30 mg immediately and then 30 mg after every hemodialysis cycle (treatment duration not to exceed 5 days) | 30 mg immediately and then 30 mg after alternate hemodialysis cycles
ESRD Patients on Continuous Ambulatory Peritoneal Dialysis [Data derived from studies in continuous ambulatory peritoneal dialysis (CAPD) patients.] (≤10 mL/minute) | A single 30 mg dose administered immediately | 30 mg immediately and then 30 mg once weekly
ESRD Patients not on Dialysis | TAMIFLU is not recommended | TAMIFLU is not recommended

2.5 Preparation and Storage of Constituted TAMIFLU Oral Suspension

Prior to dispensing to the patient, constitute TAMIFLU for oral suspension (supplied as powder):

a) Tap the closed bottle containing the supplied TAMIFLU white powder several times to loosen the powder.
b) Measure 55 mL of water in a graduated cylinder.
c) Add the total amount of water for constitution to the bottle.
d) Close bottle with child-resistant cap tightly and shake the closed bottle well for 15 seconds.
e) Label the bottle with instructions to "Shake Well Before Use".
f) The constituted oral suspension contains 360 mg of oseltamivir base per 60 mL of volume (6 mg per mL) and is white, tutti-frutti–flavored). Use the constituted oral suspension within 17 days of preparation when stored under refrigeration, 2º to 8ºC (36º to 46ºF), or within 10 days if stored at controlled room temperature, 25ºC (77ºF). Write the expiration date of the constituted oral suspension on the bottle label.
g) Ensure patients have an oral dosing dispenser that measures the appropriate volume in milliliters. Counsel patients on how to utilize the oral dosing dispenser and correctly measure the oral suspension as prescribed (see Tables 1 and 2).

2.6 Emergency Preparation of Oral Suspension from 75 mg TAMIFLU Capsules

The following directions are provided for use only during emergency situations and when FDA-approved, commercially manufactured TAMIFLU for oral suspension is not available from wholesalers or the manufacturer.

The following emergency preparation instructions will provide one patient with enough TAMIFLU for a 5-day course of treatment of influenza or a 10-day course of prophylaxis of influenza:

Step #1: Determine the dosage of TAMIFLU for the patient [see Dosage and Administration (2.2, 2.3, and 2.4)] then determine the total volume of oral suspension needed to be prepared (see Table 3).

Table 3 Emergency Preparation: Volume of Prepared Oral Suspension (6 mg per mL) Based Upon TAMIFLU Dose
TAMIFLU Dose [If the TAMIFLU dose is between the doses listed, use the greater listed dose to determine the total volume of prepared oral suspension.] | Total Volume to Prepare per Patient
15 mg or less | 37.5 mL
30 mg | 75 mL
45 mg | 100 mL
60 mg | 125 mL
75 mg | 150 mL

Step #2: Preparation must be performed with only one of the following vehicles (other vehicles have not been studied): Cherry Syrup (Humco®), Ora-Sweet® SF (sugar-free) (Paddock Laboratories), or simple syrup. Determine the number of capsules and the amount of water and vehicle needed to prepare the total volume (see Table 3) of prepared oral suspension (6 mg per mL) for a complete treatment or prophylaxis course (see Table 4).

Table 4 Emergency Preparation: Number of TAMIFLU 75 mg Capsules and Amount of Water and Vehicle Needed to Prepare the Total Volume of a Prepared Oral Suspension (6 mg per mL)
Total Volume of Prepared Oral Suspension | 37.5 mL | 75 mL | 100 mL | 125 mL | 150 mL
Number of TAMIFLU 75 mg Capsules (Total Strength) [Includes overage to ensure all doses can be delivered] | 3 (225 mg) | 6 (450 mg) | 8 (600 mg) | 10 (750 mg) | 12 (900 mg)
Amount of Water | 2.5 mL | 5 mL | 7 mL | 8 mL | 10 mL
Volume of Vehicle Cherry Syrup (Humco®) OR Ora-Sweet® SF (Paddock Laboratories) OR simple syrup | 34.5 mL | 69 mL | 91 mL | 115 mL | 137 mL

Step #3: Follow the instructions below for preparing the 75 mg TAMIFLU capsules to produce the oral suspension (6 mg per mL):

1. Place the specified amount of water into a polyethyleneterephthalate (PET) or glass bottle (see Table 4). Constitution in other bottle types is not recommended because there is no stability data with other bottle types.
2. Carefully separate the capsule body and cap and pour the contents of the required number of TAMIFLU 75 mg capsules into the PET or glass bottle.
3. Gently swirl the suspension to ensure adequate wetting of the TAMIFLU powder for at least 2 minutes.
4. Slowly add the specified amount of vehicle to the bottle.
5. Close the bottle using a child-resistant cap and shake well for 30 seconds to completely dissolve the active drug and to ensure homogeneous distribution of the dissolved drug in the resulting suspension. The active drug, oseltamivir phosphate, readily dissolves in the specified vehicles. The suspension is caused by inert ingredients of TAMIFLU capsules which are insoluble in these vehicles.
6. Put an ancillary label on the bottle indicating "Shake Well Before Use."
7. Instruct the parent or caregiver that any unused suspension remaining in the bottle following completion of therapy must be discarded by either affixing an ancillary label to the bottle or adding a statement to the pharmacy label instructions.
8. Place a pharmacy label on the bottle that includes the patient's name, dosing instructions, drug name and any other required information to be in compliance with all State and Federal Pharmacy Regulations. Place an appropriate expiration date on the label according to storage conditions below.
9. Include the recommended dosage on the pharmacy label as per Tables 1 and 2 [see Dosage and Administration (2.2, 2.3, and 2.4)].
10. Store the prepared oral suspension in glass or PET bottles either:
  - In a refrigerator [2° to 8°C (36° to 46°F)]: Stable for 5 weeks when stored in a refrigerator.
  - At room temperature [25°C (77°F)]: Stable for 5 days when stored at room temperature.

3 DOSAGE FORMS AND STRENGTHS

TAMIFLU Capsules:

- 30-mg (30 mg free base equivalent of the phosphate salt): light yellow, hard gelatin, with "ROCHE" printed in blue ink on the light yellow body and "30 mg" printed in blue ink on the light yellow cap.
- 45-mg (45 mg free base equivalent of the phosphate salt): grey, hard gelatin, with "ROCHE" printed in blue ink on the grey body and "45 mg" printed in blue ink on the grey cap.
- 75-mg (75 mg free base equivalent of the phosphate salt): grey/light yellow, hard gelatin, with "ROCHE" is printed in blue ink on the grey body and "75 mg" printed in blue ink on the light yellow cap.

TAMIFLU for Oral Suspension: 6 mg per mL (final concentration when constituted)

- White powder blend for constitution.

4 CONTRAINDICATIONS

TAMIFLU is contraindicated in patients with known serious hypersensitivity to oseltamivir or any component of the product. Severe allergic reactions have included anaphylaxis and serious skin reactions including toxic epidermal necrolysis, Stevens-Johnson Syndrome, and erythema multiforme [see Warnings and Precautions (5.1)].

5 WARNINGS AND PRECAUTIONS

5.1 Serious Skin/Hypersensitivity Reactions

Cases of anaphylaxis and serious skin reactions including toxic epidermal necrolysis, Stevens-Johnson Syndrome, and erythema multiforme have been reported in postmarketing experience with TAMIFLU. Stop TAMIFLU and institute appropriate treatment if an allergic-like reaction occurs or is suspected. The use of TAMIFLU is contraindicated in patients with known serious hypersensitivity to TAMIFLU [see Contraindications (4) and Adverse Reactions (6.2)].

5.2 Neuropsychiatric Events

There have been postmarketing reports of delirium and abnormal behavior leading to injury, and in some cases resulting in fatal outcomes, in patients with influenza who were receiving TAMIFLU [see Adverse Reactions (6.2)]. Because these events were reported voluntarily during clinical practice, estimates of frequency cannot be made but they appear to be uncommon based on TAMIFLU usage data. These events were reported primarily among pediatric patients and often had an abrupt onset and rapid resolution. The contribution of TAMIFLU to these events has not been established. Influenza can be associated with a variety of neurologic and behavioral symptoms that can include events such as hallucinations, delirium, and abnormal behavior, in some cases resulting in fatal outcomes. These events may occur in the setting of encephalitis or encephalopathy but can occur without obvious severe disease. Closely monitor TAMIFLU-treated patients with influenza for signs of abnormal behavior. If neuropsychiatric symptoms occur, evaluate the risks and benefits of continuing TAMIFLU for each patient.

5.3 Risk of Bacterial Infections

There is no evidence for efficacy of TAMIFLU in any illness caused by pathogens other than influenza viruses. Serious bacterial infections may begin with influenza-like symptoms or may coexist with or occur as complications during the course of influenza. TAMIFLU has not been shown to prevent such complications. Prescribers should be alert to the potential for secondary bacterial infections and treat them as appropriate.

5.4 Fructose Intolerance in Patients with Hereditary Fructose Intolerance

Fructose can be harmful to patients with hereditary fructose intolerance. One dose of 75 mg TAMIFLU for oral suspension delivers 2 grams of sorbitol. This is above the daily maximum limit of sorbitol for patients with hereditary fructose intolerance and may cause dyspepsia and diarrhea.

6 ADVERSE REACTIONS

The following serious adverse reactions are discussed below and elsewhere in the labeling:

- Serious skin and hypersensitivity reactions [see Warnings and Precautions (5.1)]
- Neuropsychiatric events [see Warnings and Precautions (5.2)]

6.1 Clinical Trials Experience

Because clinical trials are conducted under widely varying conditions, adverse reaction rates observed in the clinical trials of a drug cannot be directly compared to rates in the clinical trials of another drug and may not reflect the rates observed in practice.

Adverse Reactions from Treatment and Prophylaxis Trials in Adult and Adolescent Subjects (13 years of age and older)

The overall safety profile of TAMIFLU is based on data from 2,646 adult and adolescent subjects that received the recommended dosage of 75 mg orally twice daily for 5 days for treatment of influenza and 1,943 adult and adolescent subjects that received the recommended dosage of 75 mg orally once daily for up to 6 weeks for prophylaxis of influenza in clinical trials.

The most common adverse reactions in the pooled treatment and pooled prophylaxis trials in adults and adolescents are displayed in Table 5. The majority of these adverse reactions were reported on a single occasion, occurred on either the first or second treatment day and resolved spontaneously within 1-2 days. This summary includes otherwise healthy adults/adolescents and subjects "at risk" (subjects at higher risk of developing complications associated with influenza, e.g., elderly patients and patients with chronic cardiac or respiratory disease). In general, the safety profile in the subjects "at risk" was qualitatively similar to that in otherwise healthy adults/adolescents.

Table 5 Adverse Reactions Occurring in ≥1% of Adults and Adolescents (13 years of age and older) in Treatment and Prophylaxis Trials [Adverse reactions that occurred in ≥1% of TAMIFLU-treated adults and adolescents and ≥1% greater in TAMIFLU-treated subjects compared to placebo-treated subjects in either the treatment or prophylaxis trials.]
System Organ Class | Treatment Trials |  | Prophylaxis Trials
Adverse Reaction | TAMIFLU 75 mg twice daily (n = 2646) | Placebo (n = 1977) | TAMIFLU 75 mg once daily (n = 1943) | Placebo (n = 1586)
Gastrointestinal Disorders
Nausea | 10% | 6% | 8% | 4%
Vomiting | 8% | 3% | 2% | 1%
Nervous System Disorders
Headache | 2% | 1% | 17% | 16%
General Disorders
Pain | <1% | <1% | 4% | 3%

Adverse Reactions from Treatment and Prophylaxis Trials in Pediatric Subjects (1 year to 12 years of age)

A total of 1,481 pediatric subjects (including otherwise healthy pediatric subjects aged 1 year to 12 years and asthmatic pediatric subjects aged 6 to 12 years) participated in clinical trials of TAMIFLU for the treatment of influenza. A total of 859 pediatric subjects received treatment with TAMIFLU for oral suspension either at a 2 mg per kg twice daily for 5 days or weight-band dosing. Vomiting was the only adverse reaction reported at a frequency of >1% in subjects receiving TAMIFLU (16%) compared to placebo (8%).

Amongst the 148 pediatric subjects aged 1 year to 12 years who received TAMIFLU at doses of 30 to 60 mg once daily for 10 days in a post-exposure prophylaxis study in household contacts (n = 99), and in a separate 6–week seasonal influenza prophylaxis safety study (n = 49), vomiting was the most frequent adverse reaction (8% on TAMIFLU versus 2% in the no prophylaxis group).

Adverse Reactions from Treatment Trials in Pediatric Subjects (2 weeks to less than 1 year of age)

Assessment of adverse reactions in pediatric subjects 2 weeks to less than 1 year of age was based on two open-label studies that included safety data on 135 influenza-infected subjects 2 weeks to less than 1 year of age (including premature infants at least 36 weeks post conceptional age) exposed to TAMIFLU at doses ranging from 2 to 3.5 mg per kg of the formulation for oral suspension twice daily orally for 5 days. The safety profile of TAMIFLU was similar across the age range studied, with vomiting (9%), diarrhea (7%) and diaper rash (7%) being the most frequently reported adverse reactions, and was generally comparable to that observed in older pediatric and adult subjects.

Adverse Reactions from the Prophylaxis Trial in Immunocompromised Subjects

In a 12-week seasonal prophylaxis study in 475 immunocompromised subjects, including 18 pediatric subjects 1 year to 12 years of age, the safety profile in the 238 subjects receiving TAMIFLU 75 mg once daily was consistent with that previously observed in other TAMIFLU prophylaxis clinical trials [see Clinical Studies (14.2)].

6.2 Postmarketing Experience

The following adverse reactions have been identified during post-approval use of TAMIFLU. Because these reactions are reported voluntarily from a population of uncertain size, it is not possible to reliably estimate their frequency or establish a causal relationship to TAMIFLU exposure.

General disorders and administration site conditions: Swelling of the face or tongue, allergy, anaphylactic/anaphylactoid reactions, hypothermia

Skin and subcutaneous tissue disorders: Rash, dermatitis, urticaria, eczema, toxic epidermal necrolysis, Stevens-Johnson Syndrome, erythema multiforme [see Warnings and Precautions (5.1)]

Gastrointestinal Disorders: Gastrointestinal bleeding, hemorrhagic colitis

Cardiac Disorders: Arrhythmia

Hepatobiliary Disorders: Hepatitis, abnormal liver function tests

Nervous System Disorders: Seizure

Metabolism and Nutrition Disorders: Aggravation of diabetes

Psychiatric Disorders: Abnormal behavior, delirium, including symptoms such as hallucinations, agitation, anxiety, altered level of consciousness, confusion, nightmares, delusions [see Warnings and Precautions (5.2)]

7 DRUG INTERACTIONS

7.1 Influenza Vaccines

Live Attenuated Influenza Vaccine

The concurrent use of TAMIFLU with live attenuated influenza vaccine (LAIV) intranasal has not been evaluated. However, because of the potential for TAMIFLU to inhibit replication of live vaccine virus and possibly reduce the efficacy of LAIV, avoid administration of LAIV within 2 weeks before or 48 hours after TAMIFLU administration, unless medically indicated.

Inactivated Influenza Vaccine

Inactivated influenza vaccine can be administered at any time relative to use of TAMIFLU.

7.2 Drugs Without Clinically Significant Drug Interaction with TAMIFLU

No dose adjustments are needed for either oseltamivir or the concomitant drug when coadministering oseltamivir with amoxicillin, acetaminophen, aspirin, cimetidine, antacids (magnesium and aluminum hydroxides and calcium carbonates), rimantadine, amantadine, or warfarin [see Clinical Pharmacology (12.3)].

8 USE IN SPECIFIC POPULATIONS

8.1 Pregnancy

Risk Summary

There are no adequate and well-controlled studies with TAMIFLU in pregnant women to inform a drug-associated risk of adverse developmental outcomes. Available published epidemiological data suggest that TAMIFLU, taken in any trimester, is not associated with an increased risk of birth defects. However, these studies individually are limited by small sample sizes, use of different comparison groups, and some lacked information on dose, which preclude a definitive assessment of the risk [see Data and Clinical Pharmacology (12.3)]. In animal reproduction studies with oseltamivir, no adverse developmental effects were observed at clinically relevant exposures (see Data).

The background risk of major birth defects and miscarriage for the indicated populations is unknown. All pregnancies have a background risk of birth defect, loss, or other adverse outcomes. In the U.S. general population, the estimated background risk of major birth defects and miscarriage is 2-4% and 15-20%, respectively.

Clinical Considerations

Disease-Associated Maternal and/or Embryo/Fetal Risk

Pregnant women are at higher risk of severe complications from influenza, which may lead to adverse pregnancy and/or fetal outcomes including maternal death, still births, birth defects, preterm delivery, low birth weight and small for gestational age.

Data

Human Data

Published prospective and retrospective observational studies of more than 5,000 women exposed to TAMIFLU during pregnancy, including more than 1,000 women exposed in the first trimester, suggest that the observed rate of congenital malformations was not increased above the rate in the general comparison population, regardless of when therapy was administered during the gestational period. However, individually, none of these studies had adequate sample sizes and some lacked information on dose, which preclude a definitive assessment of the risk.

Animal Data

Oseltamivir was administered orally during organogenesis to pregnant rats (at 50, 250, or 1500 mg/kg/day on gestation days 6 to 17) and rabbits (at 50, 150, or 500 mg/kg/day on gestation days 6 to 18). In rats, embryo-fetal effects consisting of an increased incidence of minor skeletal malformations were observed at a maternally toxic dose (1500 mg/kg/day), resulting in systemic drug exposures (based on AUC for oseltamivir carboxylate) 190 times human exposures at the maximum recommended human dose (MRHD) of TAMIFLU (75 mg twice a day). In the rabbit study, embryo-fetal effects consisting of an increased incidence of minor skeletal abnormalities and variants were observed at maternally toxic doses (≥150 mg/kg/day) resulting in systemic exposures (based on AUC for oseltamivir carboxylate) ≥8 times human exposures at the MRHD of TAMIFLU.

In prenatal and postnatal development studies in rats, oseltamivir was administered orally (at 50, 250, 500, or 1500 mg/kg/day) from organogenesis through late gestation, delivery, and lactation (gestation day 6 to postpartum/lactation day 20). Prolonged parturition duration and reduced offspring viability were observed at a maternally toxic dose (1500 mg/kg/day). No adverse maternal or offspring effects were observed at doses ≤500 mg/kg/day, resulting in systemic drug exposures (based on AUC for oseltamivir carboxylate) 44 times human exposures at the MRHD of TAMIFLU.

8.2 Lactation

Risk Summary

Based on limited published data, oseltamivir and oseltamivir carboxylate have been shown to be present in human milk at low levels considered unlikely to lead to toxicity in the breastfed infant. Postmarketing experience has not reported any information to suggest serious adverse effects of oseltamivir exposure via breast milk in infants. It is not known if oseltamivir affects human milk production. The developmental and health benefits of breastfeeding should be considered along with the mother's clinical need for TAMIFLU and any potential adverse effects on the breastfed child from the drug or from the underlying maternal condition.

8.4 Pediatric Use

Treatment of Influenza

The safety and efficacy of TAMIFLU for the treatment of influenza in pediatric patients 2 weeks old to 17 years of age has been established [see Dosage and Administration (2.2), Clinical Pharmacology (12.3), and Clinical Studies (14.1)] and is based on:

- 13 to 17 years of age: Safety and efficacy in adolescent patients 13 to 17 years of age was supported by adequate and well-controlled trials in adults and adolescents and younger pediatric patients and safety data in adolescents treated with TAMIFLU in a study of treatment and prophylaxis.
- 1 year to 12 years of age: Safety and efficacy in pediatric patients 1 year to 12 years of age was supported by results of one double-blind, placebo-controlled trial in 452 pediatric patients with influenza in whom TAMIFLU 2 mg per kg twice daily or placebo was administered within 48 hours of symptom onset [see Clinical Studies (14.1)]. Additional safety information was provided in a double-blind, placebo-controlled trial in pediatric patients 6 to 12 years of age with known asthma. Efficacy could not be established in pediatric patients with asthma.
- 2 weeks to less than 1 year of age: Safety and efficacy in pediatric patients 2 weeks to less than 1 year of age is supported by adequate and well-controlled trials in adults and older pediatric patients and two open-label trials of TAMIFLU (2 to 3.5 mg per kg twice daily for 5 days) in 136 pediatric subjects 2 weeks to less than 1 year of age. In these two trials, the oseltamivir plasma concentrations in these subjects were similar to or higher than the oseltamivir plasma concentrations observed in older pediatric subjects and adults [see Clinical Pharmacology (12.3) and Clinical Studies (14.1)].

The safety and efficacy of TAMIFLU for treatment of influenza in pediatric patients less than 2 weeks of age have not been established.

Prophylaxis of Influenza

The safety and efficacy of TAMIFLU for the prophylaxis of influenza in pediatric patients 1 year to 17 years old has been established [see Dosage and Administration (2.3), Clinical Pharmacology (12.3), and Clinical Studies (14.2)] and is based on:

- 13 to 17 years of age: Prophylaxis in adolescent patients 13 to 17 years of age is supported by one randomized, placebo-controlled post-exposure household prophylaxis trial of TAMIFLU 75 mg taken orally once daily for 7 days in household contacts including 207 adolescents [see Clinical Studies (14.2)].
- 1 year to 12 years of age: TAMIFLU for prophylaxis in pediatric patients 1 year to 12 years of age is supported by one randomized, open-label, post-exposure household prophylaxis trial including pediatric subjects 1 year to 12 years of age who received 30 to 60 mg of TAMIFLU for oral suspension (supplied as powder) taken orally once daily for 10 days [see Clinical Studies (14.2)]. Additional safety information was provided in a 6-week seasonal prophylaxis (community outbreak) safety study in 49 patients 1 year to 12 years of age.

The safety and efficacy of TAMIFLU for prophylaxis of influenza have not been established for pediatric patients less than 1 year of age.

8.5 Geriatric Use

Treatment of Influenza

Of the 4,765 adults in clinical trials of TAMIFLU for the treatment of influenza, 948 (20%) were 65 years and older, while 329 (7%) were 75 years and older. In three double-blind, placebo-controlled trials in the treatment of influenza in patients at least 65 years old, that enrolled 741 subjects (374 received placebo and 362 received TAMIFLU), no overall differences in safety or effectiveness were observed between these subjects and younger subjects, and other reported clinical experience has not identified differences in responses between the elderly and younger subjects [see Clinical Studies (14.1)].

Prophylaxis of Influenza

Of the 4,603 adults in clinical trials of TAMIFLU for the prophylaxis of influenza, 1,046 (23%) were 65 years and older, while 719 (16%) were 75 years and older. In a randomized, placebo-controlled trial in elderly residents of nursing homes who took TAMIFLU for up to 42 days for the prophylaxis of influenza (TAMIFLU n=276, placebo n=272), no overall differences in safety or effectiveness were observed between these subjects and younger subjects, and other reported clinical experience has not identified differences in responses between the elderly and younger subjects [see Clinical Studies (14.2)].

8.6 Renal Impairment

Patients with renal impairment had higher blood levels of oseltamivir carboxylate compared to patients with normal renal function which may increase the risk of TAMIFLU-associated adverse reactions. Therefore, dosage adjustment is recommended for patients with a serum creatinine clearance between 10 and 60 mL/minute and for patients with end-stage renal disease (ESRD) undergoing routine hemodialysis or continuous peritoneal dialysis treatment [see Dosage and Administration (2.4)]. TAMIFLU is not recommended for patients with ESRD not undergoing dialysis [see Indications and Usage (1.3) and Clinical Pharmacology (12.3)].

8.7 Hepatic Impairment

No dosage adjustment is required in patients with mild to moderate hepatic impairment. The safety and pharmacokinetics in patients with severe hepatic impairment have not been evaluated [see Clinical Pharmacology (12.3)].

8.8 Use in Patients with Chronic Conditions

Efficacy of TAMIFLU in the treatment of influenza in patients with chronic cardiac disease and/or respiratory disease was evaluated in one randomized, placebo-controlled clinical trial. Efficacy in this population, as measured by time to alleviation of all symptoms, was not established, but no new safety signals were identified [see Clinical Studies (14.1)].

No clinical trial data are available regarding treatment of influenza in patients with any medical condition sufficiently severe or unstable to be considered at imminent risk of requiring hospitalization.

8.9 Immunocompromised Patients

Efficacy of TAMIFLU for the treatment or prophylaxis of influenza has not been established in immunocompromised patients [see Clinical Studies (14.2)]. Safety of TAMIFLU has been demonstrated for up to 12 weeks for prophylaxis of influenza in immunocompromised patients [see Adverse Reactions (6.1)].

10 OVERDOSAGE

Reports of overdoses with TAMIFLU have been received from clinical trials and during postmarketing experience. In the majority of cases reporting overdose, no adverse reactions were reported. Adverse reactions reported following overdose were similar in nature to those observed with therapeutic doses of TAMIFLU [see Adverse Reactions (6)].

11 DESCRIPTION

TAMIFLU (oseltamivir phosphate), an influenza neuraminidase inhibitor (NAI), is available as:

- Capsules containing 30 mg, 45 mg, or 75 mg of oseltamivir for oral use, in the form of oseltamivir phosphate, and
- A powder for oral suspension, which when constituted with water as directed contains 6 mg per mL oseltamivir base.

In addition to the active ingredient, each capsule contains croscarmellose sodium, povidone K30, pregelatinized starch, sodium stearyl fumarate and talc. The 30 mg capsule shell contains gelatin, red iron oxide, titanium dioxide, and yellow iron oxide. The 45 mg capsule shell contains black iron oxide, gelatin, and titanium dioxide. The 75 mg capsule shell contains black iron oxide, gelatin, red iron oxide, titanium dioxide, and yellow iron oxide. Each capsule is printed with blue ink, which includes FD&C Blue No. 2 as the colorant.

In addition to the active ingredient, the powder for oral suspension contains monosodium citrate, saccharin sodium, sodium benzoate, sorbitol, titanium dioxide, tutti-frutti flavoring, and xanthan gum.

Oseltamivir phosphate is a white crystalline solid with the chemical name (3R,4R,5S)-4-acetylamino-5-amino-3(1-ethylpropoxy)-1-cyclohexene-1-carboxylic acid, ethyl ester, phosphate (1:1). The chemical formula is C16H28N2O4 (free base). The molecular weight is 312.4 for oseltamivir free base and 410.4 for oseltamivir phosphate salt. The structural formula is as follows:

12 CLINICAL PHARMACOLOGY

12.1 Mechanism of Action

Oseltamivir is an antiviral drug with activity against influenza virus [see Microbiology (12.4)].

12.3 Pharmacokinetics

Absorption and Bioavailability

Oseltamivir is absorbed from the gastrointestinal tract after oral administration of TAMIFLU (oseltamivir phosphate) and is extensively converted predominantly by hepatic esterases to oseltamivir carboxylate. At least 75% of an oral dose reaches the systemic circulation as oseltamivir carboxylate and less than 5% of the oral dose reaches the systemic circulation as oseltamivir (see Table 6).

Table 6 Mean (% CV) Pharmacokinetic Parameters of Oseltamivir and Oseltamivir Carboxylate Following Multiple Dosing of 75 mg Capsules Twice Daily (n=20)
Parameter | Oseltamivir | Oseltamivir Carboxylate
Cmax (ng/mL) | 65 (26) | 348 (18)
AUC0-12h (ng∙h/mL) | 112 (25) | 2719 (20)

Plasma concentrations of oseltamivir carboxylate are proportional to doses up to 500 mg given twice daily (about 6.7 times the maximum recommended TAMIFLU dosage) [see Dosage and Administration (2)].

Coadministration with food had no significant effect on the peak plasma concentration (551 ng/mL under fasted conditions and 441 ng/mL under fed conditions) and the area under the plasma concentration time curve (6218 ng∙h/mL under fasted conditions and 6069 ng∙h/mL under fed conditions) of oseltamivir carboxylate.

Distribution

The volume of distribution (Vss) of oseltamivir carboxylate, following intravenous administration in 24 subjects (TAMIFLU is not available as an IV formulation), ranged between 23 and 26 liters.

The binding of oseltamivir carboxylate to human plasma protein is low (3%). The binding of oseltamivir to human plasma protein is 42%, which is insufficient to cause significant displacement-based drug interactions.

Elimination

Absorbed oseltamivir is primarily (>90%) eliminated by conversion to the active metabolite, oseltamivir carboxylate. Plasma concentrations of oseltamivir declined with a half-life of 1 to 3 hours in most subjects after oral administration. Oseltamivir carboxylate is not further metabolized and is eliminated unchanged in urine. Plasma concentrations of oseltamivir carboxylate declined with a half-life of 6 to 10 hours in most subjects after oral administration.

Metabolism

Oseltamivir is extensively converted to the active metabolite, oseltamivir carboxylate, by esterases located predominantly in the liver. Oseltamivir carboxylate is not further metabolized. Neither oseltamivir nor oseltamivir carboxylate is a substrate for, or inhibitor of, cytochrome P450 isoforms.

Excretion

Oseltamivir carboxylate is eliminated entirely (>99%) by renal excretion. Renal clearance (18.8 L/h) exceeds glomerular filtration rate (7.5 L/h), indicating that tubular secretion (via organic anion transporter) occurs in addition to glomerular filtration. Less than 20% of an oral radiolabeled dose is eliminated in feces.

Specific Populations

Renal Impairment

Administration of 100 mg of TAMIFLU twice daily (about 1.3 times the maximum recommended dosage) for 5 days to subjects with various degrees of renal impairment showed that exposure to oseltamivir carboxylate is inversely proportional to declining renal function.

Population-derived pharmacokinetic parameters were determined for patients with varying degrees of renal function including ESRD patients on hemodialysis. Median simulated exposures of oseltamivir carboxylate for recommended treatment and prophylaxis regimens are provided in Table 7. The pharmacokinetics of oseltamivir have not been studied in ESRD patients not undergoing dialysis [see Indications and Usage (1.3), and Use in Specific Populations (8.6)].

Table 7 Simulated Median Treatment Exposure Metrics of Oseltamivir Carboxylate in Patients with Normal Renal Function, with Renal Impairment and ESRD Patients on Hemodialysis
Renal Function/Impairment | Normal Creatinine Clearance 90-140 mL/min (n=57) | Mild Creatinine Clearance 60-90 mL/min (n=45) | Moderate Creatinine Clearance 30-60 mL/min (n=13) | Severe Creatinine Clearance 10-30 mL/min (n=11) | ESRD Creatinine Clearance <10 mL/min on Hemodialysis (n=24)
Recommended Treatment Regimens
PK exposure parameter | 75 mg twice daily | 75 mg twice daily | 30 mg twice daily | 30 mg once daily | 30 mg every HD cycle
Cmin (ng/mL) | 145 | 253 | 180 | 219 | 221
Cmax (ng/mL) | 298 | 464 | 306 | 477 | 1170
AUC48 (ng∙h/mL) [AUC normalized to 48 hours.] | 11224 | 18476 | 12008 | 16818 | 23200
Recommended Prophylaxis Regimens
PK exposure parameter | 75 mg once daily | 75 mg once daily | 30 mg once daily | 30 mg every other day | 30 mg alternate HD cycle
Cmin (ng/mL) | 39 | 62 | 57 | 70 | 42
Cmax (ng/mL) | 213 | 311 | 209 | 377 | 903
AUC48 (ng∙hr/mL) | 5294 | 8336 | 6262 | 9317 | 11200

In continuous ambulatory peritoneal dialysis (CAPD) patients, the peak concentration of oseltamivir carboxylate following a single 30 mg dose of oseltamivir or once weekly oseltamivir was approximately 3-fold higher than in patients with normal renal function who received 75 mg twice daily. The plasma concentration of oseltamivir carboxylate on Day 5 (147 ng/mL) following a single 30 mg dose in CAPD patients is similar to the predicted Cmin (160 ng/mL) in patients with normal renal function following 75 mg twice daily. Administration of 30 mg once weekly to CAPD patients resulted in plasma concentrations of oseltamivir carboxylate at the 168 hour blood sample of 63 ng/mL, which were comparable to the Cmin in patients with normal renal function receiving the approved regimen of 75 mg once daily (40 ng/mL).

Hepatic Impairment

In clinical studies, oseltamivir carboxylate exposure was not altered in subjects with mild or moderate hepatic impairment [see Use in Specific Populations (8.7)].

Pregnant Women

A pooled population pharmacokinetic analysis indicates that the TAMIFLU dosage regimen resulted in lower exposure to the active metabolite in pregnant women (n=59) compared to non-pregnant women (n=33). However, this predicted exposure is expected to have activity against susceptible influenza virus strains and there are insufficient pharmacokinetics and safety data to recommend a dose adjustment for pregnant women [see Use in Specific Populations (8.1)].

Pediatric Subjects (1 year to 12 years of age)

The pharmacokinetics of oseltamivir and oseltamivir carboxylate have been evaluated in a single-dose pharmacokinetic study in pediatric subjects aged 5 to 16 years (n=18) and in a small number of pediatric subjects aged 3 to 12 years (n=5) enrolled in a clinical trial. Younger pediatric subjects cleared both the prodrug and the active metabolite faster than adult subjects resulting in a lower exposure for a given mg/kg dose. For oseltamivir carboxylate, apparent total clearance decreases linearly with increasing age (up to 12 years). The pharmacokinetics of oseltamivir in pediatric subjects over 12 years of age are similar to those in adult subjects [see Use in Specific Populations (8.4)].

Pediatric Subjects (2 weeks to less than 1 year of age)

The pharmacokinetics of oseltamivir and oseltamivir carboxylate have been evaluated in two open-label studies of pediatric subjects less than one year of age (n=122) infected with influenza. Apparent clearance of the active metabolite decreases with decreasing age in subjects less than 1 year of age; however the oseltamivir and oseltamivir carboxylate exposure following a 3 mg/kg dose in subjects under 1 year of age is expected to be within the observed exposures in adults and adolescents receiving 75 mg twice daily and 150 mg twice daily [see Use in Specific Populations (8.4)].

Geriatric Patients

Exposure to oseltamivir carboxylate at steady-state was 25 to 35% higher in geriatric subjects (age range 65 to 78 years) compared to young adults given comparable doses of oseltamivir. Half-lives observed in the geriatric subjects were similar to those seen in young adults. Based on drug exposure and tolerability, dose adjustments are not required for geriatric patients for either treatment or prophylaxis [see Use in Specific Populations (8.5)].

Drug Interaction Studies

Oseltamivir is extensively converted to oseltamivir carboxylate by esterases, located predominantly in the liver. Drug interactions involving competition for esterases have not been extensively reported in literature. Low protein binding of oseltamivir and oseltamivir carboxylate suggests that the probability of drug displacement interactions is low.

In vitro studies demonstrate that neither oseltamivir nor oseltamivir carboxylate is a good substrate for P450 mixed-function oxidases or for glucuronyl transferases.

Coadministration of probenecid results in an approximate two-fold increase in exposure to oseltamivir carboxylate due to a decrease in active anionic tubular secretion in the kidney. However, due to the safety margin of oseltamivir carboxylate, no dose adjustments are required when coadministering with probenecid.

No clinically relevant pharmacokinetic interactions have been observed when coadministering oseltamivir with amoxicillin, acetaminophen, aspirin, cimetidine, antacids (magnesium and aluminum hydroxides and calcium carbonates), rimantadine, amantadine, or warfarin.

12.4 Microbiology

Mechanism of Action

Oseltamivir phosphate is an ethyl ester prodrug requiring ester hydrolysis for conversion to the active form, oseltamivir carboxylate. Oseltamivir carboxylate is an inhibitor of influenza virus neuraminidase affecting release of viral particles. The median IC50 values of oseltamivir against influenza A/H1N1, influenza A/H3N2, and influenza B clinical isolates were 2.5 nM (range 0.93-4.16 nM, N=74), 0.96 nM (range 0.13-7.95 nM, N=774), and 60 nM (20-285 nM, N=256), respectively, in a neuraminidase assay with a fluorescently labeled MUNANA substrate.

Antiviral Activity

The antiviral activity of oseltamivir carboxylate against laboratory strains and clinical isolates of influenza virus was determined in cell culture. The concentrations of oseltamivir carboxylate required for inhibition of influenza virus in cell culture were highly variable depending on the assay method used and the virus tested. The 50% and 90% effective concentrations (EC50 and EC90) were in the range of 0.0008 micromolar to greater than 35 micromolar and 0.004 micromolar to greater than 100 micromolar, respectively (1 micromolar=0.284 microgram per mL). The relationship between the antiviral activity in cell culture, inhibitory activity in the neuraminidase assay, and the inhibition of influenza virus replication in humans has not been established.

Resistance

Cell culture studies: Influenza A virus isolates with reduced susceptibility to oseltamivir carboxylate have been recovered by serial passage of virus in cell culture in the presence of increasing concentrations of oseltamivir carboxylate. Reduced susceptibility of influenza virus to inhibition by oseltamivir carboxylate may be conferred by amino acid substitutions in the viral neuraminidase and/or hemagglutinin proteins.

Clinical studies: Reduced susceptibility isolates have been obtained during treatment with oseltamivir and from sampling during community surveillance studies. Changes in the viral neuraminidase that have been associated with reduced susceptibility to oseltamivir carboxylate are summarized in Table 8. The clinical impact of this reduced susceptibility is unknown.

Hemagglutinin (HA) substitutions selected in cell culture and associated with reduced susceptibility to oseltamivir include (influenza virus subtype-specific numbering) A11T, K173E, and R453M in H3N2; and H99Q in influenza B virus (Yamagata lineage). In some cases, HA substitutions were selected in conjunction with known NA resistance substitutions and may contribute to reduced susceptibility to oseltamivir; however, the impact of HA substitutions on antiviral activity of oseltamivir in humans is unknown and likely to be strain-dependent.

Table 8 Neuraminidase Amino Acid Substitutions Associated with Reduced Susceptibility to Oseltamivir

Amino Acid Substitution [All numbering is N2, except where indicated.]

Influenza A N1 (N1 numbering in brackets)

I117V (I117V), E119V (E119V), R152K (R152K), Y155H (Y155H), F173V (F174V), D198G/N (D199G/N), I222K/R/T/V (I223K/R/T/V), S246G/N (S247G/N), G248R+I266V (G249R+I267V), H274Y (H275Y), N294S (N295S), Q312R+I427T (Q313R+I427T), N325K (N325K), R371K (R368K)

Influenza A N2

E41G, E119I/V, D151V, I222L/V, Q226H, SASG245-248 deletion, S247P, R292K, N294S

Influenza B (B numbering in brackets)

E119A (E117A), P141S (P139S), G142R (G140R), R152K (R150K), D198E/N/Y (D197E/N/Y), I222L/T/V (I221L/T/V), A246D/S/T (A245D/S/T), H274Y (H273Y), N294S (N294S), R371K (R374K), G402S (G407S)

Selection of influenza A viruses resistant to oseltamivir can occur at higher frequencies in children. Oseltamivir treatment-associated resistance in pediatric treatment studies has been detected at frequencies of 27 to 37% and 3 to 18% (3/11 to 7/19 and 1/34 to 9/50 post-treatment isolates, respectively) for influenza A/H1N1 virus and influenza A/H3N2 virus, respectively.

In immunocompromised adults and pediatrics (1 year of age and older), selection of influenza viruses resistant to oseltamivir can occur at higher frequencies than in the otherwise healthy population. In a treatment study of immunocompromised subjects, treatment-associated genotypic resistance was detected in 27% (8/30), 12% (6/52), and 0% (0/42) of influenza A/H1N1, A/H3N2, and B virus infections, respectively. Treatment-emergent resistance was observed at a higher frequency in hematopoietic stem cell transplant recipients (32%; 6/19).

The frequency of resistance selection to oseltamivir and the prevalence of such resistant virus vary seasonally and geographically.

Circulating seasonal influenza strains expressing neuraminidase resistance-associated substitutions have been observed in individuals who have not received oseltamivir treatment. The oseltamivir resistance-associated substitution H275Y was found in more than 99% of US-circulating 2008 H1N1 influenza virus isolates. The 2009 H1N1 influenza virus ("swine flu") was almost uniformly susceptible to oseltamivir; however, the frequency of circulating resistant variants can change from season to season. Prescribers should consider available information from the CDC on influenza virus drug susceptibility patterns and treatment effects when deciding whether to use TAMIFLU.

Cross-resistance

Cross-resistance between oseltamivir and zanamivir has been observed in neuraminidase biochemical assays. The H275Y (N1 numbering) or N294S (N2 numbering) oseltamivir resistance-associated substitutions observed in the N1 neuraminidase subtype, and the E119V or N294S oseltamivir resistance-associated substitutions observed in the N2 subtype (N2 numbering), are associated with reduced susceptibility to oseltamivir but not zanamivir. The Q136K and K150T zanamivir resistance-associated substitutions observed in N1 neuraminidase, or the S250G zanamivir resistance-associated substitutions observed in influenza B virus neuraminidase, confer reduced susceptibility to zanamivir but not oseltamivir. The R292K oseltamivir resistance-associated substitution observed in N2, and the I222T, D198E/N, R371K, or G402S oseltamivir resistance-associated substitutions observed in influenza B virus neuraminidase, confer reduced susceptibility to both oseltamivir and zanamivir. These examples do not represent an exhaustive list of cross resistance-associated substitutions and prescribers should consider available information from the CDC on influenza drug susceptibility patterns and treatment effects when deciding whether to use TAMIFLU.

No single amino acid substitution has been identified that could confer cross-resistance between the neuraminidase inhibitor class (oseltamivir, zanamivir) and the M2 ion channel inhibitor class (amantadine, rimantadine). However, a virus may carry a neuraminidase inhibitor-associated substitution in neuraminidase and an M2 ion channel inhibitor-associated substitution in M2 and may therefore be resistant to both classes of inhibitors. The clinical relevance of phenotypic cross-resistance evaluations has not been established.

Immune Response

No influenza vaccine/oseltamivir interaction study has been conducted. In studies of naturally acquired and experimental influenza, treatment with TAMIFLU did not impair normal humoral antibody response to infection.

13 NONCLINICAL TOXICOLOGY

13.1 Carcinogenesis, Mutagenesis, Impairment of Fertility

In 2-year carcinogenicity studies in mice and rats given daily oral doses of the prodrug oseltamivir phosphate up to 400 mg/kg and 500 mg/kg, respectively, the prodrug and the active form oseltamivir carboxylate induced no statistically significant increases in tumors over controls. The mean maximum daily exposures to the prodrug in mice and rats were approximately 130- and 320-fold, respectively, greater than those in humans at the recommended clinical dose based on AUC comparisons. The respective safety margins of the exposures to the active oseltamivir carboxylate were 15- and 50-fold.

Oseltamivir was found to be non-mutagenic in the Ames test and the human lymphocyte chromosome assay with and without enzymatic activation and negative in the mouse micronucleus test. It was found to be positive in a Syrian Hamster Embryo (SHE) cell transformation test. Oseltamivir carboxylate was non-mutagenic in the Ames test and the L5178Y mouse lymphoma assay with and without enzymatic activation and negative in the SHE cell transformation test.

In a fertility and early embryonic development study in rats, doses of oseltamivir at 50, 250, and 1500 mg/kg/day were administered to females for 2 weeks before mating, during mating and until day 6 of pregnancy. Males were dosed for 4 weeks before mating, during mating, and for 2 weeks after mating. There were no effects on fertility, mating performance or early embryonic development at any dose level. The highest dose in this study was approximately 115 times the human systemic exposure (AUC0-24h) of oseltamivir carboxylate that occurs after administration of the maximum recommended human dose.

14 CLINICAL STUDIES

14.1 Treatment of Influenza

Adults

Two randomized, placebo-controlled, double-blind clinical trials of TAMIFLU were conducted in adults between 18 and 65 years old, one in the U.S. and one outside the U.S., for the treatment of acute uncomplicated influenza. Eligible subjects had fever of at least 100ºF, accompanied by at least one respiratory symptom (cough, nasal symptoms, or sore throat) and at least one systemic symptom (myalgia, chills/sweats, malaise, fatigue, or headache), and influenza virus was known to be circulating in the community. Subjects were randomized to receive oral TAMIFLU or placebo for 5 days. All enrolled subjects were allowed to take fever-reducing medications.

Of 1,355 subjects enrolled in these two trials, 849 (63%) subjects were influenza-infected (median age 34 years; 52% male; 90% Caucasian; 31% smokers). Of the 849 influenza-infected subjects, 95% were infected with influenza A, 3% with influenza B, and 2% with influenza of unknown type.

Study medication was started within 40 hours of onset of symptoms and administered twice daily for 5 days. Subjects were required to self-assess the influenza-associated symptoms (nasal congestion, sore throat, cough, aches, fatigue, headaches, and chills/sweats) twice daily as "none," "mild," "moderate," or "severe". Time to improvement was calculated from the time of treatment initiation to the time when all symptoms were assessed as "none" or "mild". In both trials, there was a 1.3-day reduction in the median time to improvement in influenza-infected subjects who received TAMIFLU 75 mg twice a day for 5 days compared to subjects who received placebo. Subgroup analyses by gender showed no differences in the treatment effect of TAMIFLU in men and women.

In the treatment of influenza, no increased efficacy was demonstrated in subjects who received higher doses of TAMIFLU.

Adolescents and Adults with Chronic Cardiac or Respiratory Disease

A double-blind, placebo-controlled, multicenter trial was unable to demonstrate efficacy of TAMIFLU (75 mg twice daily for 5 days) in the treatment of influenza in adult and adolescent subjects (13 years or older) with chronic cardiac (excluding chronic idiopathic hypertension) or respiratory diseases, as measured by time to alleviation of all symptoms. However, in patients treated with TAMIFLU there was a more rapid cessation of febrile illness. No difference in the incidence of influenza complications was observed between the treatment and placebo groups in this population.

Geriatric Subjects

Three double-blind placebo-controlled treatment trials were conducted in subjects who were at least 65 years of age in three consecutive seasons. The enrollment criteria were similar to that of adult trials with the exception of fever being defined as higher than 97.5°F. Of 741 subjects enrolled, 476 (65%) subjects were influenza-infected; of these, 95% were infected with influenza type A and 5% with influenza type B.

In the pooled analysis, there was a 1-day reduction in the median time to improvement in influenza-infected subjects who received TAMIFLU 75 mg twice daily for 5 days compared to those who received placebo (p=NS) [see Use in Specific Populations (8.5)]. Some seasonal variability was noted in the clinical efficacy outcomes.

Pediatric Subjects (1 year to 12 years of age)

One double-blind placebo-controlled treatment trial was conducted in pediatric subjects aged 1 year to 12 years (median age 5 years) who had fever (at least 100ºF) plus one respiratory symptom (cough or coryza) when influenza virus was known to be circulating in the community. Of 698 subjects enrolled in this trial, 452 (65%) were influenza-infected (50% male; 68% Caucasian). Of the 452 influenza-infected subjects, 67% were infected with influenza A and 33% with influenza B.

Efficacy in this trial was determined by the time to alleviation or resolution of influenza signs and symptoms, measured by a composite endpoint that required the following four individual conditions be met: i) alleviation of cough, ii) alleviation of coryza, iii) resolution of fever, and iv) parental opinion of a return to normal health and activity. TAMIFLU treatment of 2 mg per kg twice daily, started within 48 hours of onset of symptoms, reduced the total composite time to freedom from illness by 1.5 days compared to placebo. Subgroup analyses by gender showed no differences in the treatment effect of TAMIFLU in male and female pediatric subjects.

Pediatric Subjects (2 weeks to less than 1 year of age)

Two open-label trials evaluated the safety and pharmacokinetics of oseltamivir and oseltamivir carboxylate in influenza-infected pediatric subjects 2 weeks to less than 1 year of age (including premature infants at least 36 weeks post conceptional age). Subjects received TAMIFLU at doses ranging from 2 to 3.5 mg per kg twice daily for 5 days depending on subject age. These clinical trials were not designed to evaluate clinical efficacy or virologic response.

Of the 136 subjects under the age of 1 year enrolled and dosed in the trials, the majority of the subjects were male (55%), white (79%), non-Hispanic (74%), full term (76%) and infected with influenza A (80%). Pharmacokinetic data indicated that a dose of 3 mg per kg twice daily in pediatric subjects 2 weeks to less than 1 year of age provided TAMIFLU concentrations similar to or higher than those observed in older pediatric subjects and adults receiving the approved dose and provided the basis for approval [see Adverse Reactions (6.1) and Use in Specific Populations (8.4)].

14.2 Prophylaxis of Influenza

Adult and Adolescent Subjects (13 years of age and older)

The efficacy of TAMIFLU in preventing naturally occurring influenza illness has been demonstrated in three seasonal prophylaxis (community outbreak) clinical trials and one post-exposure prophylaxis trial in household contacts. The efficacy endpoint for all of these trials was the incidence of laboratory-confirmed clinical influenza defined as meeting all the following criteria (all signs and symptoms must have been recorded within 24 hours):

- oral temperature greater than or equal to 99.0ºF (37.2ºC),
- at least one respiratory symptom (cough, sore throat, nasal congestion),
- at least one constitutional symptom (aches and pain, fatigue, headache, chills/sweats), and
- either a positive virus isolation or a four-fold increase in virus antibody titers from baseline.

In a pooled analysis of two seasonal prophylaxis trials in healthy unvaccinated adults (aged 18 to 65 years), TAMIFLU 75 mg once daily taken for 42 days during a community outbreak reduced the incidence of laboratory-confirmed clinical influenza from 5% (25/519) for the placebo group to 1% (6/520) for the TAMIFLU group.

In the seasonal (community outbreak) prophylaxis trial in elderly residents of skilled nursing homes, about 80%, 43%, and 14% of the subjects were vaccinated, had cardiac disorders, and had chronic airway obstructive disorders, respectively. In this trial, subjects were randomized to TAMIFLU 75 mg once daily or placebo taken orally for 42 days. The incidence of laboratory-confirmed clinical influenza was 4% (12/272) in the placebo-treated subjects compared to less than 1% (1/276) in the TAMIFLU-treated subjects.

In the post-exposure prophylaxis trial in household contacts (aged 13 years or older) of an index influenza case, TAMIFLU 75 mg once daily or placebo taken orally was administered within 48 hours of onset of symptoms in the index case and continued for 7 days (index cases did not receive TAMIFLU treatment). The incidence of laboratory-confirmed clinical influenza was 12% (24/200) in the placebo-treated subjects compared to 1% (2/205) in the TAMIFLU-treated subjects.

Pediatric Subjects (1 year to 12 years of age)

The efficacy of TAMIFLU in preventing naturally occurring influenza illness was demonstrated in a randomized, open-label post-exposure prophylaxis trial in household contacts that included pediatric subjects aged 1 year to 12 years, both as index cases and as family contacts. All index cases in this trial received TAMIFLU for oral suspension 30 to 60 mg taken orally once daily for 10 days. The efficacy parameter was the incidence of laboratory-confirmed clinical influenza in the household. Laboratory-confirmed clinical influenza was defined as meeting all of the following criteria:

- oral temperature at least 100°F (37.8°C),
- cough and/or coryza recorded within 48 hours, and
- either a positive virus isolation or a four-fold or greater increase in virus antibody titers from baseline or at illness visits.

Among household contacts 1 year to 12 years of age not already shedding virus at baseline, the incidence of laboratory-confirmed clinical influenza was lower in the group who received TAMIFLU prophylaxis [3% (3/95)] compared to the group who did not receive TAMIFLU prophylaxis [17% (18/106)].

Immunocompromised Subjects

A double-blind, placebo-controlled trial was conducted for seasonal prophylaxis of influenza in 475 immunocompromised subjects (including 18 pediatric subjects 1 year to 12 years of age) who had received solid organ (n=388; liver, kidney, liver and kidney) or hematopoietic stem cell transplants (n=87). Median time since transplant for solid organ transplant recipients was 1,105 days for the placebo group and 1,379 days for the TAMIFLU group. Median time since transplant for hematopoietic stem cell transplant recipients was 424 days for the placebo group and 367 days for the TAMIFLU group. Approximately 40% of subjects received influenza vaccine prior to entering the study. The primary efficacy endpoint was the incidence of confirmed clinical influenza, defined as oral temperature higher than 99.0°F (37.2°C) plus cough and/or coryza, all recorded within 24 hours, plus either a positive virus culture or a four-fold increase in virus antibody titers from baseline. Subjects received treatment with TAMIFLU 75 mg or placebo once daily by mouth for 12 weeks. The incidence of confirmed clinical influenza was 3% (7/238) in the placebo group compared with 2% (5/237) in the TAMIFLU group; this difference was not statistically significant. A secondary analysis was performed using the same clinical symptoms and RT-PCR for laboratory confirmation of influenza infection. Among subjects who were not already shedding virus at baseline, the incidence of RT-PCR-confirmed clinical influenza infection was 3% (7/231) in the placebo group and <1% (1/232) in the TAMIFLU group.

16 HOW SUPPLIED/STORAGE AND HANDLING

TAMIFLU Capsules

30-mg capsules (30 mg free base equivalent of the phosphate salt): light yellow hard gelatin capsules. "ROCHE" is printed in blue ink on the light yellow body and "30 mg" is printed in blue ink on the light yellow cap. Available in blister packages of 10 (NDC 0004-0802-85).

45-mg capsules (45 mg free base equivalent of the phosphate salt): grey hard gelatin capsules. "ROCHE" is printed in blue ink on the grey body and "45 mg" is printed in blue ink on the grey cap. Available in blister packages of 10 (NDC 0004-0801-85).

75-mg capsules (75 mg free base equivalent of the phosphate salt): grey/light yellow hard gelatin capsules. "ROCHE" is printed in blue ink on the grey body and "75 mg" is printed in blue ink on the light yellow cap. Available in blister packages of 10 (NDC 0004-0800-85).

Storage

Store the capsules at 25ºC (77ºF); excursions permitted to 15º to 30ºC (59º to 86ºF) [See USP Controlled Room Temperature].

TAMIFLU for Oral Suspension (Supplied as Powder)

Supplied as a white powder blend in a glass bottle. After constitution, the powder blend produces a white tutti-frutti–flavored oral suspension. After constitution with 55 mL of water, each bottle delivers a usable volume of 60 mL of oral suspension equivalent to 360 mg oseltamivir base (6 mg/mL) [see Dosage and Administration (2.5)] (NDC 0004-0822-05).

Storage

Store dry powder at 25ºC (77ºF); excursions permitted to 15º to 30ºC (59º to 86ºF) [See USP Controlled Room Temperature].

Store constituted oral suspension under refrigeration for up to 17 days at 2º to 8ºC (36º to 46ºF). Do not freeze. Alternatively, store constituted oral suspension for up to 10 days at 25ºC (77ºF); excursions permitted to 15º to 30ºC (59º to 86ºF) [See USP Controlled Room Temperature].

17 PATIENT COUNSELING INFORMATION

Advise the patient to read the FDA-approved patient labeling (Patient Information and Instructions for Use).

Serious Skin/Hypersensitivity Reactions

Advise patients and/or caregivers of the risk of severe allergic reactions (including anaphylaxis) or serious skin reactions. Instruct patients and/or caregiver to stop TAMIFLU and seek immediate medical attention if an allergic-like reaction occurs or is suspected [see Warnings and Precautions (5.1)].

Neuropsychiatric Events

Advise patients and/or caregivers of the risk of neuropsychiatric events in TAMIFLU-treated patients with influenza and instruct patients to contact their physician if they experience signs of abnormal behavior while receiving TAMIFLU [see Warnings and Precautions (5.2)].

Important Dosing Information

Instruct patients to begin treatment with TAMIFLU as soon as possible from the first appearance of flu symptoms, within 48 hours of onset of symptoms. Similarly, instruct patients to start taking TAMIFLU for prevention as soon as possible after exposure [see Dosage and Administration (2)]. Instruct patients to take any missed doses as soon as they remember, except if it is near the next scheduled dose (within 2 hours), and then continue to take TAMIFLU at the usual times.

Influenza Vaccines

Instruct patients that TAMIFLU is not a substitute for receiving an annual flu vaccination. Patients should continue receiving an annual flu vaccination according to guidelines on immunization practices. Because of the potential for TAMIFLU to inhibit replication of live attenuated influenza vaccine (LAIV) and possibly reduce efficacy of LAIV, avoid administration of LAIV within 2 weeks or 48 hours after TAMIFLU administration, unless medically necessary [see Drug Interactions (7.1)].

Fructose Intolerance

Inform patients with hereditary fructose intolerance that one dose of 75 mg TAMIFLU oral suspension (supplied as powder) delivers 2 grams of sorbitol. Inform patients with hereditary fructose intolerance that this is above the daily maximum limit of sorbitol and may cause dyspepsia and diarrhea [see Warnings and Precautions (5.4)].

Distributed by:
Genentech, Inc.
A Member of the Roche Group
1 DNA Way
South San Francisco, CA 94080-4990
©2019 Genentech, Inc. All rights reserved

Licensor:
Gilead Sciences, Inc.
Foster City, California 94404

PATIENT INFORMATION

TAMIFLU® (TAM-ih-flew)
(oseltamivir phosphate)
capsules, for oral use

TAMIFLU® (TAM-ih-flew)
(oseltamivir phosphate)
for oral suspension

What is TAMIFLU?

TAMIFLU is a prescription medicine used to:

- treat the flu (influenza) in people 2 weeks of age and older who have had flu symptoms for no more than two days.
- prevent the flu in people who are 1 year of age and older.

It is not known if TAMIFLU is:

- effective in people who start treatment after 2 days of developing flu symptoms.
- effective for the treatment of the flu in people with long-time (chronic) heart problems or breathing problems.
- effective for the treatment or prevention of flu in people who have weakened immune systems (immunocompromised)
- safe and effective for the treatment of the flu in children less than 2 weeks of age.
- safe and effective in the prevention of the flu in children less than 1 year of age.

TAMIFLU does not treat or prevent illness that is caused by infections other than the influenza virus.

TAMIFLU does not prevent bacterial infections that may happen with the flu.

TAMIFLU is not recommended for people with end-stage renal disease (ESRD) who are not receiving dialysis.

TAMIFLU does not take the place of receiving a flu vaccination. Talk to your healthcare provider about when you should receive an annual flu vaccination.

Who should not take TAMIFLU?

Do not take TAMIFLU if you are allergic to oseltamivir phosphate or any of the ingredients in TAMIFLU. See the end of this leaflet for a complete list of ingredients in TAMIFLU.

What should I tell my healthcare provider before taking TAMIFLU?

Before you take TAMIFLU, tell your healthcare provider if you:

- have problems swallowing TAMIFLU capsules
- have kidney problems
- have a history of fructose (fruit sugar) intolerance. TAMIFLU contains sorbitol and may cause stomach upset and diarrhea in people who are fructose intolerant.
- have any other medical conditions
- are pregnant or plan to become pregnant. Available information indicate that TAMIFLU does not increase the risk of birth defects.
- are breastfeeding or plan to breastfeed. TAMIFLU can pass into breast milk in small amounts.

Tell your healthcare provider about all the medicines you take, including prescription or over-the-counter medicines, vitamins, and herbal supplements.

Know the medicines you take. Keep a list of them to show your healthcare provider and pharmacist when you get a new medicine.

How should I take TAMIFLU?

- Take TAMIFLU exactly as your healthcare provider tells you to.
- Take TAMIFLU with food or without food. There is less chance of stomach upset if you take TAMIFLU with food.
- If you miss a dose of TAMIFLU, take it as soon as you remember. If it is 2 hours or less before your next dose, do not take the missed dose. Take your next dose of TAMIFLU at your scheduled time. Do not take 2 doses at the same time.
- If TAMIFLU for oral suspension is not available or you cannot swallow TAMIFLU capsules, your healthcare provider or pharmacist may instruct you to open TAMIFLU capsules and mix the capsules contents with sweetened liquids such as chocolate syrup (regular or sugar-free), corn syrup, caramel topping, or light brown sugar (dissolved in water).
- If your healthcare provider or pharmacist has instructed you to take TAMIFLU for oral suspension or open your TAMIFLU capsules, read the detailed Instructions for Use at the end of this leaflet. Ask your pharmacist if you have any questions.

What are the possible side effects of TAMIFLU?

TAMIFLU may cause serious side effects, including:

- Serious skin and allergic reactions. TAMIFLU can cause serious skin and allergic reactions. Stop taking TAMIFLU and get medical help right away if you get any of the following symptoms:

- skin rash or hives
- your skin blisters and peels
- blisters or sores in your mouth
- itching

- swelling of your face, eyes, lips, tongue, or throat
- trouble breathing
- chest pain or tightness

- Change in behavior. People, especially children, who have the flu, can develop nervous system problems and abnormal behavior that can lead to death. During treatment with TAMIFLU, tell your healthcare provider right away if you or your child have confusion, speech problems, shaky movements, seizures, or start hearing voices or seeing things that are not really there (hallucinations).

The most common side effects of TAMIFLU when used for treatment of the flu include nausea, vomiting, and headache.

The most common side effect of TAMIFLU when used for prevention of the flu include nausea, vomiting, headache, and pain.

Tell your healthcare provider if you have any side effect that bothers you or that does not go away.

These are not all of the possible side effects of TAMIFLU.

Call your doctor for medical advice about side effects. You may report side effects to FDA at 1-800-FDA-1088.

How should I store TAMIFLU?

- Store TAMIFLU capsules at room temperature between 68°F to 77°F (20°C to 25°C).
- Store TAMIFLU for oral suspension in the refrigerator for up to 17 days between 36ºF to 46ºF (2ºC to 8ºC) Do not freeze.
- Store TAMIFLU for oral suspension for up to 10 days at room temperature between 68°F to 77°F (20°C to 25°C).
- Safely throw away any unused TAMIFLU that is out of date or no longer needed.

Keep TAMIFLU and all medicines out of the reach of children.

General information about the safe and effective use of TAMIFLU.

Medicines are sometimes prescribed for purposes other than those listed in a Patient Information leaflet. Do not use TAMIFLU for a condition for which it was not prescribed. Do not give TAMIFLU to other people, even if they have the same symptoms you have. It may harm them. If you would like more information, talk with your healthcare provider. You can ask your healthcare provider or pharmacist for information about TAMIFLU that is written for health professionals. For more information, go to www.tamiflu.com.

What are the ingredients in TAMIFLU?

Active ingredient: oseltamivir phosphate

Inactive ingredients:

TAMIFLU capsules: croscarmellose sodium, povidone K30, pregelatinized starch, sodium stearyl fumarate, and talc

30mg capsule shell: gelatin, red iron oxide, titanium dioxide, and yellow iron oxide

45mg capsules shell: black iron oxide, gelatin, and titanium dioxide

75mg capsules shell: black iron oxide, gelatin, red iron oxide, titanium dioxide, and yellow iron oxide

TAMIFLU for oral suspension: monosodium citrate, saccharin sodium, sodium benzoate, sorbitol, titanium dioxide, tutti-frutti flavoring, and xanthan gum.

Distributed by: Genentech, Inc., A Member of the Roche Group, 1 DNA Way, South San Francisco, CA 94080-4990
Licensor: Gilead Sciences, Inc., Foster City, California, 94404
©2019 Genentech, Inc. All rights reserved

This Patient Information has been approved by the U.S. Food and Drug Administration.

Revised 08/2019

INSTRUCTIONS FOR USE
 | TAMIFLU® (TAM-ih-flew) (oseltamivir phosphate) capsules, for oral use | TAMIFLU® (TAM-ih-flew) (oseltamivir phosphate) for oral suspension
How do I give a dose of TAMIFLU for oral suspension?
Step 1. | Shake the TAMIFLU for oral suspension bottle well before each use.
Step 2. | Open the bottle by pushing downward on the child resistant bottle cap and twisting it in the direction of the arrow.
Step 3. | Measure the oral suspension with an appropriate oral dosing dispenser to be sure you get the correct dose. Contact your pharmacist if you do not have an appropriate oral dosing dispenser.
Step 4. | Give the full contents of oral dosing dispenser directly into the mouth.
Step 5. | Close the bottle with the child-resistant bottle cap after each use.
Step 6. | Rinse oral dosing dispenser under running tap water and allow to air dry after each use.
How do I mix the contents of TAMIFLU capsules with sweetened liquids, if directed by my healthcare provider or pharmacist?
You will need:
 | - the prescribed dose of TAMIFLU capsules - a small bowl - sweetened liquid, such as chocolate syrup (regular or sugar-free), corn syrup, caramel topping, or light brown sugar (dissolved in water)
Step 1. | Open the contents of the prescribed dose of TAMIFLU capsules into a small bowl.
Step 2. | Add a small amount of the sweetened liquid to the capsule contents.
Step 3. | Stir the mixture and give the entire dose of TAMIFLU.
This Instructions for Use has been approved by the U.S. Food and Drug Administration. |  |  | Revised 06/2016

Representative sample of labeling (see the HOW SUPPLIED section for complete listing):

PRINCIPAL DISPLAY PANEL - 30 mg Capsule Blister Pack Carton

NDC 0004-0802-85

Tamiflu®
(oseltamivir phosphate) Capsules

30 mg

Each capsule contains oseltamivir phosphate equivalent to 30 mg
oseltamivir (free base).

Rx only

10 Capsules

Genentech

10175386

PRINCIPAL DISPLAY PANEL - 45 mg Capsule Blister Pack Carton

NDC 0004-0801-85

Tamiflu®
(oseltamivir phosphate) Capsules

45 mg

Each capsule contains oseltamivir phosphate equivalent to 45 mg
oseltamivir (free base).

Rx only

10 Capsules

Genentech

10175387

PRINCIPAL DISPLAY PANEL - 75 mg Capsule Blister Pack Carton

NDC 0004-0800-85

Tamiflu®
(oseltamivir phosphate) Capsules

75 mg

Each capsule contains oseltamivir phosphate equivalent to 75 mg
oseltamivir (free base).

Rx only

10 Capsules

Genentech

11026905

PRINCIPAL DISPLAY PANEL - 60 mL Bottle Carton

NDC 0004-0822-05

Tamiflu®
(oseltamivir phosphate)
for Oral Suspension

6 mg/mL

Each mL contains 6 mg
oseltamivir base after
constitution.

60 mL (usable volume
after constitution)

Rx only

Genentech

10240835